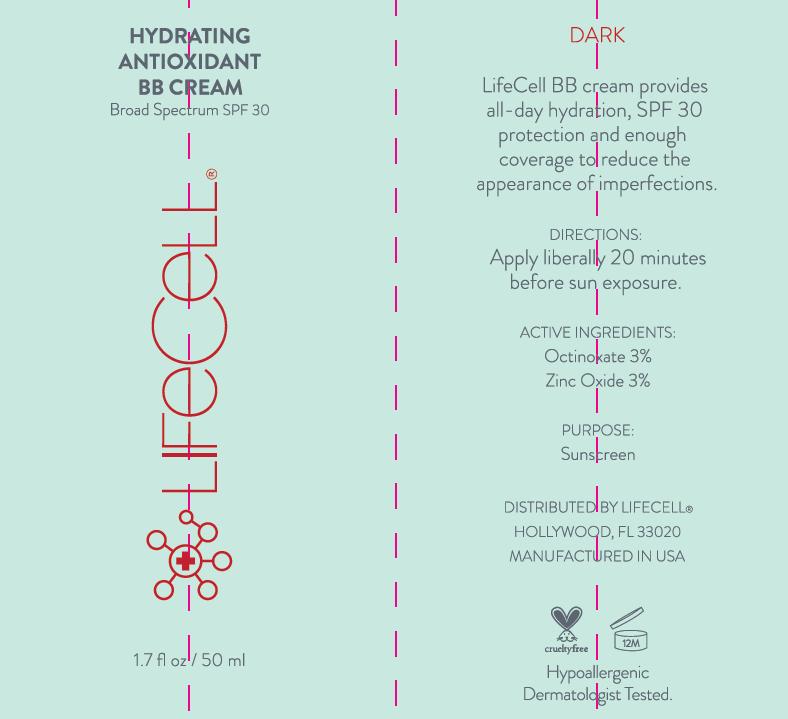 DRUG LABEL: Lifecell
NDC: 58443-0191 | Form: CREAM
Manufacturer: Prime Enterprises Inc.
Category: otc | Type: HUMAN OTC DRUG LABEL
Date: 20200117

ACTIVE INGREDIENTS: ZINC OXIDE 29.01 mg/1 mL; OCTINOXATE 29.01 mg/1 mL
INACTIVE INGREDIENTS: TITANIUM DIOXIDE; SODIUM CHLORIDE; ALMOND OIL; SILICON DIOXIDE; GREEN TEA LEAF; BENTONITE; CARAMEL; CETYL DIMETHICONE 45; CETYL PEG/PPG-10/1 DIMETHICONE (HLB 2); CHOLECALCIFEROL; HIGH DENSITY POLYETHYLENE; CYCLOMETHICONE 5; CYCLOMETHICONE 6; PROPYLENE GLYCOL; DMDM HYDANTOIN; HEXYL LAURATE; HYDROGENATED CASTOR OIL; FERRIC OXIDE RED; ISOCETYL STEARATE; MELANIN SYNTHETIC (TYROSINE, PEROXIDE); WATER; ALOE VERA LEAF; ALPHA-TOCOPHEROL ACETATE; EDETATE DISODIUM; OCTYL STEARATE; POLYGLYCERYL-4 ISOSTEARATE

Lifecell BB Cream Broad Spectrum SPF 30

DARK

Uses

LifeCell BB cream provides all-day hydration, SPF 30 protection and enough coverage to reduce the appearance of imperfections.

Directions

Apply liberally 20 minutes before sun exposure.

Active Ingredients

Octinoxate 3%

Zinc Oxide 3%

PURPOSE

Sunscreen

OTHER SAFETY INFORMATION

Hypoallergenic

Dermatologist Tested